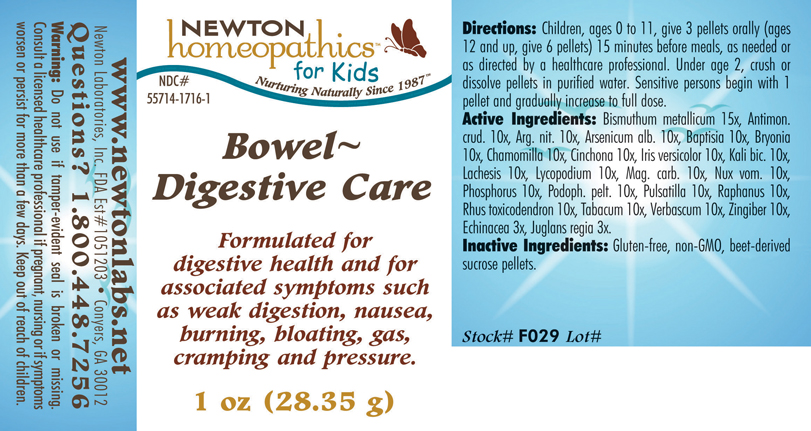 DRUG LABEL: Bowel Digestive Care 
NDC: 55714-1716 | Form: PELLET
Manufacturer: Newton Laboratories, Inc.
Category: homeopathic | Type: HUMAN OTC DRUG LABEL
Date: 20110301

ACTIVE INGREDIENTS: Bismuth 15 [hp_X]/1 g; Antimony Trisulfide 10 [hp_X]/1 g; Silver Nitrate 10 [hp_X]/1 g; Arsenic Trioxide 10 [hp_X]/1 g; Baptisia Tinctoria 10 [hp_X]/1 g; Bryonia Alba Root 10 [hp_X]/1 g; Matricaria Recutita 10 [hp_X]/1 g; Cinchona Officinalis Bark 10 [hp_X]/1 g; Iris Versicolor Root 10 [hp_X]/1 g; Potassium Dichromate 10 [hp_X]/1 g; Lachesis Muta Venom 10 [hp_X]/1 g; Lycopodium Clavatum Spore 10 [hp_X]/1 g; Magnesium Carbonate 10 [hp_X]/1 g; Strychnos Nux-vomica Seed 10 [hp_X]/1 g; Phosphorus 10 [hp_X]/1 g; Podophyllum 10 [hp_X]/1 g; Pulsatilla Vulgaris 10 [hp_X]/1 g; Daikon 10 [hp_X]/1 g; Toxicodendron Pubescens Leaf 10 [hp_X]/1 g; Tobacco Leaf 10 [hp_X]/1 g; Verbascum Thapsus 10 [hp_X]/1 g; Ginger 10 [hp_X]/1 g; Echinacea, Unspecified 3 [hp_X]/1 g; Juglans Regia Leaf 3 [hp_X]/1 g
INACTIVE INGREDIENTS: Sucrose

Bowel - Digestive Care

INDICATIONS & USAGE SECTION

Bowel - Digestive Care Formulated for digestive health and for associated symptoms such as weak digestion, nausea, burning, bloating, gas, cramping and pressure.

DOSAGE & ADMINISTRATION SECTION

Directions: Children, ages 0 to 11, give 3 pellets orally (ages 12 and up, give 6 pellets) 15 minutes before meals, as needed or as directed by a healthcare professional. Under age 2, crush or dissolve pellets in purified water. Sensitive persons begin with 1 pellet and gradually increase to full dose.

OTC - ACTIVE INGREDIENT SECTION

Bismuthum metallicum 15x, Antimon.crud. 10x, Arg. nit. 10x, Arsenicum alb. 10x, Baptisia 10x, Bryonia 10x, Chamomilla 10x, Cinchona 10x, Iris versicolor 10x, Kali bic. 10x, Lachesis 10x, Lycopodium 10x, Mag. carb. 10x, Nux vom. 10x, Phosphorus 10x, Podoph. pelt. 10x, Pulsatilla 10x, Raphanus 10x, Rhus toxicodendron 10x, Tabacum 10x, Verbascum 10x, Zingiber 10x, Echinacea 3x, Juglans regia 3x.

OTC - PURPOSE SECTION

Formulated for digestive health and for associated symptoms such as weak digestion, nausea, burning, bloating, gas, cramping and pressure.

INACTIVE INGREDIENT SECTION

Inactive Ingredients: Gluten-free, non-GMO, beet-derived sucrose pellets.

QUESTIONS SECTION

www.newtonlabs.net Newton Laboratories, Inc. FDA Est # 1051203 - Conyers, GA 30012
Questions? 1.800.448.7256

WARNINGS SECTION

Warning: Do not use if tamper - evident seal is broken or missing. Consult a licensed healthcare professional if pregnant, nursing or if symptoms worsen or persist for more than a few days. Keep out of reach of children.

OTC - PREGNANCY OR BREAST FEEDING SECTION

Consult a licensed healthcare professional if pregnant, nursing or if symptoms worsen or persist for more than a few days.

OTC - KEEP OUT OF REACH OF CHILDREN SECTION

Keep out of reach of children.